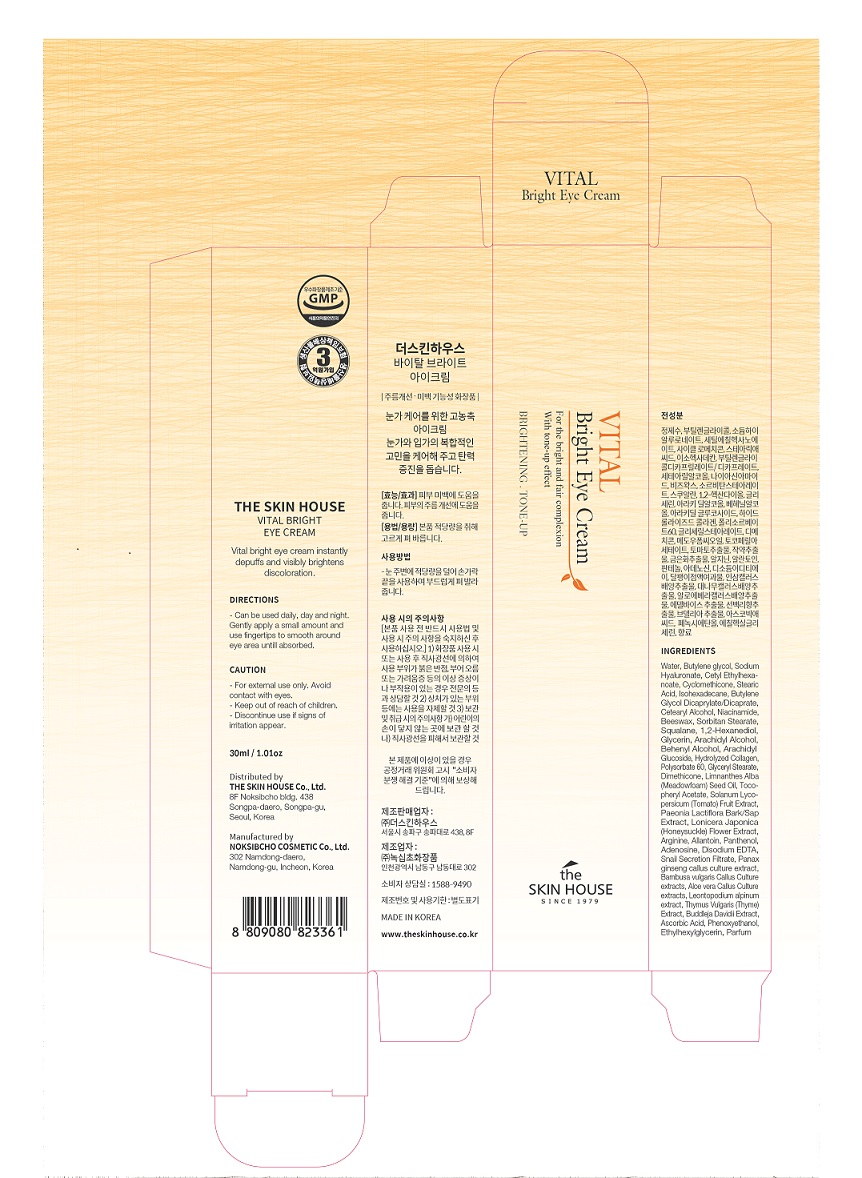 DRUG LABEL: THE SKIN HOUSE Vital Bright EyeCream
NDC: 73590-0027 | Form: CREAM
Manufacturer: NOKSIBCHO cosmetic Co., Ltd.
Category: otc | Type: HUMAN OTC DRUG LABEL
Date: 20200330

ACTIVE INGREDIENTS: NIACINAMIDE 2 g/100 mL
INACTIVE INGREDIENTS: WATER

Drug Facts

ACTIVE INGREDIENT

Niacinamide

INACTIVE INGREDIENT

Water
Butylene glycol
Sodium Hyaluronate
Cetyl Ethylhexanoate
Cyclomethicone
Stearic Acid
Isohexadecane
Butylene Glycol Dicaprylate/Dicaprate
Cetearyl Alcohol
Beeswax
Sorbitan Stearate
Squalane
1,2-Hexanediol
Glycerin
Arachidyl Alcohol
Behenyl Alcohol
Arachidyl Glucoside
Hydrolyzed Collagen
Polysorbate 60
Glyceryl Stearate
Dimethicone
Limnanthes Alba (Meadowfoam) Seed Oil
Tocopheryl Acetate
Solanum Lycopersicum (Tomato) Fruit Extract
Paeonia Lactiflora Extract
Lonicera Japonica (Honeysuckle) Flower Extract
Arginine
Allantoin
Panthenol
Disodium EDTA
Snail Secretion Filtrate
Panax ginseng callus culture extract
Bambusa vulgaris Callus Culture extracts
Aloe vera Callus Culture extracts
Leontopodium alpinum extract
Thymus Vulgaris (Thyme) Extract
Buddleja Davidii Extract
Ascorbic Acid
Phenoxyethanol
Ethylhexylglycerin
Parfum

PURPOSE

skin brightening

keep out of reach of the children

INDICATIONS AND USAGE

apply proper amount to the skin

WARNINGS

For external use only
When using this product

■ if the following symptoms occurs after use, stop use and consult with a skin specialist

red specks, swelling, itching

■ don’t use on the part where there is injury, eczema, or dermatitis

Keep out of reach of children

■ if swallowed, get medical help or contact a person control center immediately